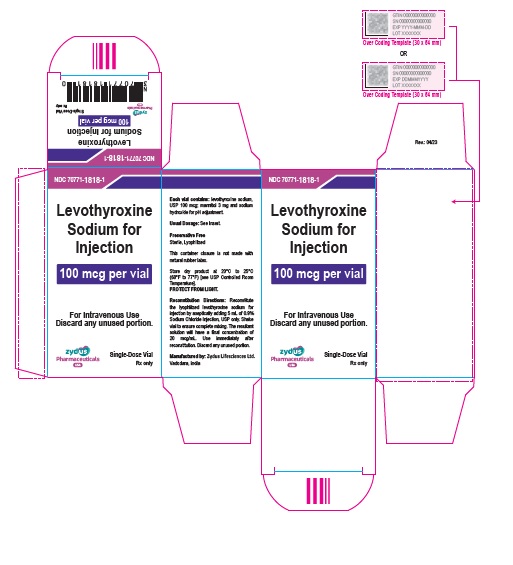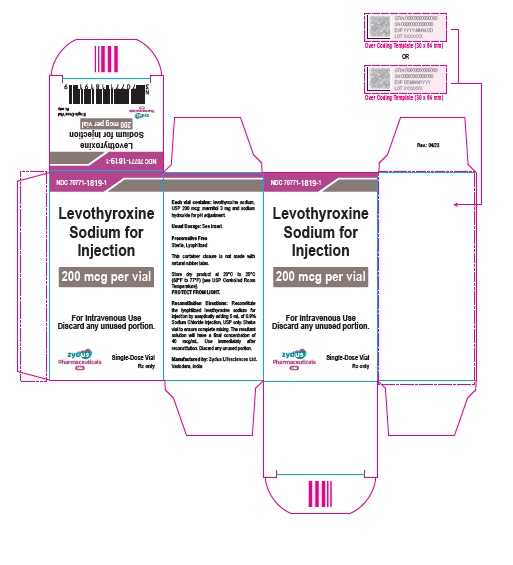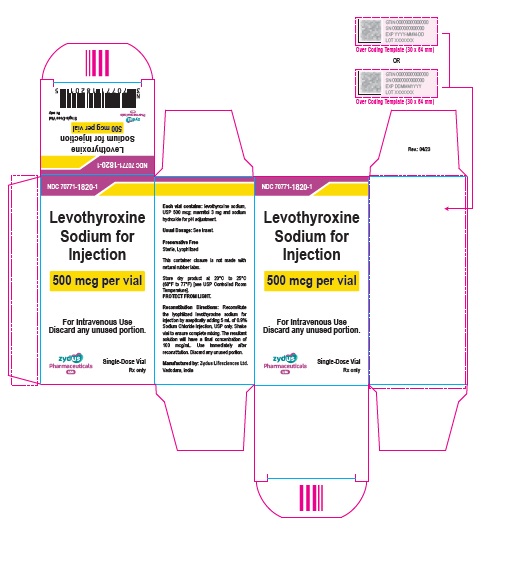 DRUG LABEL: LEVOTHYROXINE SODIUM
NDC: 70771-1818 | Form: INJECTION, POWDER, LYOPHILIZED, FOR SOLUTION
Manufacturer: Zydus Lifesciences Limited
Category: prescription | Type: HUMAN PRESCRIPTION DRUG LABEL
Date: 20241024

ACTIVE INGREDIENTS: LEVOTHYROXINE SODIUM ANHYDROUS 100 ug/5 mL
INACTIVE INGREDIENTS: MANNITOL; SODIUM HYDROXIDE

Levothyroxine Sodium for Injection

PACKAGE LABEL.PRINCIPAL DISPLAY PANEL

NDC 70771-1818-1

Levothyroxine Sodium for Injection

100 mcg per vial

For Intravenous Use

Discard any unused portion

Single-Dose Vial

Rx only

NDC 70771-1819-1

Levothyroxine Sodium for Injection

200 mcg per vial

For Intravenous Use

Discard any unused portion

Single-Dose Vial

Rx only

NDC 70771-1820-1

Levothyroxine Sodium for Injection

500 mcg per vial

For Intravenous Use

Discard any unused portion

Single-Dose Vial

Rx only